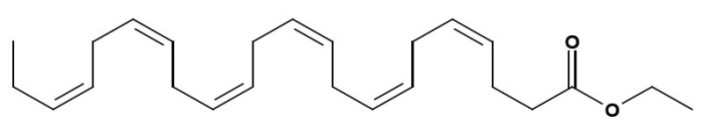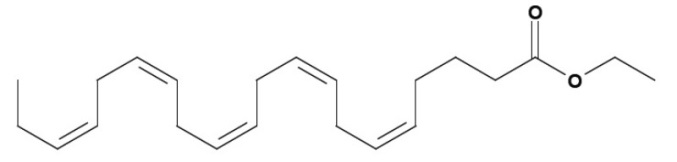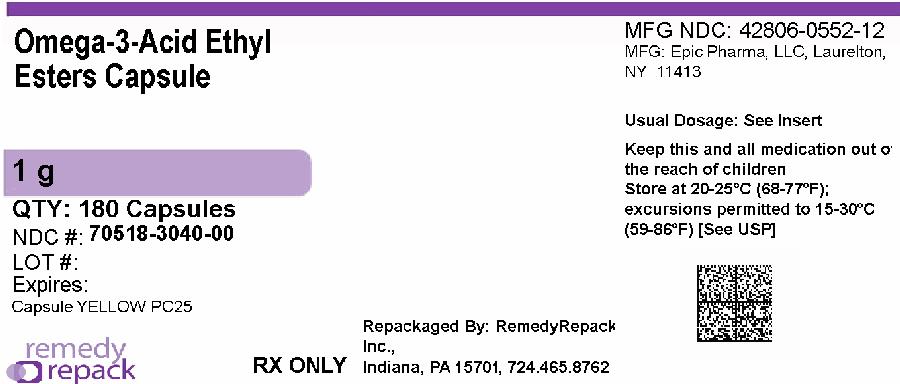 DRUG LABEL: OMEGA-3-ACID ETHYL ESTERS
NDC: 70518-3040 | Form: CAPSULE, LIQUID FILLED
Manufacturer: REMEDYREPACK INC.
Category: prescription | Type: HUMAN PRESCRIPTION DRUG LABEL
Date: 20260218

ACTIVE INGREDIENTS: OMEGA-3-ACID ETHYL ESTERS 1 g/1 1
INACTIVE INGREDIENTS: GELATIN, UNSPECIFIED; GLYCERIN; WATER; PROPYLENE GLYCOL; SHELLAC; TITANIUM DIOXIDE

HIGHLIGHTS OF PRESCRIBING INFORMATION

These highlights do not include all the information needed to use OMEGA-3-ACID ETHYL ESTERS CAPSULES safely and effectively. See full prescribing information for OMEGA-3-ACID ETHYL ESTERS CAPSULES.
Initial U.S. Approval: 2004

1 INDICATIONS AND USAGE

Omega-3-acid ethyl esters capsules are a combination of ethyl esters of omega 3 fatty acids, principally eicosapentaenoic acid (EPA) and docosahexaenoic acid (DHA),, indicated as an adjunct to diet to reduce triglyceride (TG) levels in adult patients with severe (≥500 mg/dL) hypertriglyceridemia. (1)

Limitations of Use:

- The effect of omega-3-acid ethyl esters capsules on the risk for pancreatitis has not been determined. (1)
- The effect of omega-3-acid ethyl esters capsules on cardiovascular mortality and morbidity has not been determined. (1)

2 DOSAGE AND ADMINISTRATION

- The daily dose of omega-3-acid ethyl esters capsules is 4 grams per day taken as a single 4-gram dose (4 capsules) or as two 2-gram doses (2 capsules given twice daily). (2)
- Patients should be advised to swallow omega-3-acid ethyl esters capsules whole. Do not break open, crush, dissolve, or chew omega-3-acid ethyl esters capsules. (2)

3 DOSAGE FORMS AND STRENGTHS

Capsules: 1 gram (3)

4 CONTRAINDICATIONS

Omega-3-acid ethyl esters capsules are contraindicated in patients with known hypersensitivity (e.g., anaphylactic reaction) to omega-3-acid ethyl esters or any of its components. (4)

5 WARNINGS AND PRECAUTIONS

- In patients with hepatic impairment, monitor ALT and AST levels periodically during therapy. (5.1)
- Omega-3-acid ethyl esters may increase levels of low-density lipoprotein (LDL). Monitor LDL levels periodically during therapy. (5.1)
- Use with caution in patients with known hypersensitivity to fish and/or shellfish. (5.2)
- There is a possible association between omega-3-acid ethyl esters and more frequent recurrences of symptomatic atrial fibrillation or flutter in patients with paroxysmal or persistent atrial fibrillation, particularly within the first months of initiating therapy. (5.3)

6 ADVERSE REACTIONS

The most common adverse reactions (incidence >3% and greater than placebo) were eructation, dyspepsia, and taste perversion. (6)

To report SUSPECTED ADVERSE REACTIONS, contact [Epic Pharma LLC at 1-888-374-2791] or FDA at 1-800-FDA-1088 or www.fda.gov/medwatch.

7 DRUG INTERACTIONS

Omega-3-acids may prolong bleeding time. Patients taking omega-3-acid ethyl esters and an anticoagulant or other drug affecting coagulation (e.g., anti-platelet agents) should be monitored periodically. (7.1)

FULL PRESCRIBING INFORMATION

1 INDICATIONS AND USAGE

Omega-3-acid ethyl esters capsules are indicated as an adjunct to diet to reduce triglyceride (TG) levels in adult patients with severe (greater than or equal to 500 mg/dL) hypertriglyceridemia.

Usage Considerations:Patients should be placed on an appropriate lipid-lowering diet before receiving omega-3-acid ethyl esters capsules and should continue this diet during treatment with omega-3-acid ethyl esters capsules.

Laboratory studies should be done to ascertain that the lipid levels are consistently abnormal before instituting therapy with omega-3-acid ethyl esters capsules. Every attempt should be made to control serum lipids with appropriate diet, exercise, weight loss in obese patients, and control of any medical problems such as diabetes mellitus and hypothyroidism that are contributing to the lipid abnormalities. Medications known to exacerbate hypertriglyceridemia (such as beta blockers, thiazides, estrogens) should be discontinued or changed if possible prior to consideration of TG-lowering drug therapy.

Limitations of Use:

The effect of omega-3-acid ethyl esters capsules on the risk for pancreatitis has not been determined.

The effect of omega-3-acid ethyl esters capsules on cardiovascular mortality and morbidity has not been determined.

2 DOSAGE AND ADMINISTRATION

- Assess TG levels carefully before initiating therapy. Identify other causes (e.g., diabetes mellitus, hypothyroidism, medications) of high TG levels and manage as appropriate [see Indications and Usage (1)].
- Patients should be placed on an appropriate lipid-lowering diet before receiving omega-3-acid ethyl esters capsules, and should continue this diet during treatment with omega-3-acid ethyl esters capsules. In clinical studies, omega-3-acid ethyl esters capsules was administered with meals.

The daily dose of omega-3-acid ethyl esters capsules is 4 grams per day. The daily dose may be taken as a single 4-gram dose (4 capsules) or as two 2-gram doses (2 capsules given twice daily).

Patients should be advised to swallow omega-3-acid ethyl esters capsules whole. Do not break open, crush, dissolve, or chew omega-3-acid ethyl esters capsules.

3 DOSAGE FORMS AND STRENGTHS

Omega-3-acid ethyl esters capsules USP are supplied as 1 gram oblong, clear, soft gelatin capsules filled with light yellow liquid and imprinted with "PC25" in white ink.

4 CONTRAINDICATIONS

Omega-3-acid ethyl esters capsules are contraindicated in patients with known hypersensitivity (e.g., anaphylactic reaction) to omega-3-acid ethyl esters or any of its components.

5 WARNINGS AND PRECAUTIONS

5.1 Monitoring: Laboratory Tests

In patients with hepatic impairment, alanine aminotransferase (ALT) and aspartate aminotransferase (AST) levels should be monitored periodically during therapy with omega-3-acid ethyl esters. In some patients, increases in ALT levels without a concurrent increase in AST levels were observed.

In some patients, omega-3-acid ethyl esters increases low-density lipoprotein cholesterol (LDL-C) levels. LDL-C levels should be monitored periodically during therapy with omega-3-acid ethyl esters.

Laboratory studies should be performed periodically to measure the patient’s TG levels during therapy with omega-3-acid ethyl esters.

5.2 Fish Allergy

Omega-3-acid ethyl esters contains ethyl esters of omega-3 fatty acids (EPA and DHA) obtained from the oil of several fish sources. It is not known whether patients with allergies to fish and/or shellfish, are at increased risk of an allergic reaction to omega-3-acid ethyl esters. Omega-3-acid ethyl esters should be used with caution in patients with known hypersensitivity to fish and/or shellfish.

5.3 Recurrent Atrial Fibrillation (AF) or Flutter

In a double-blind, placebo-controlled trial of 663 subjects with symptomatic paroxysmal AF (n = 542) or persistent AF (n = 121), recurrent AF or flutter was observed in subjects randomized to omega-3-acid ethyl esters who received 8 grams per day for 7 days and 4 grams/day thereafter for 23 weeks at a higher rate relative to placebo. Subjects in this trial had median baseline TG levels of 127 mg/dL, had no substantial structural heart disease, were taking no anti-arrhythmic therapy (rate control permitted), and were in normal sinus rhythm at baseline.

At 24 weeks, in the paroxysmal AF stratum, there were 129 (47%) first recurrent symptomatic AF or flutter events on placebo and 141 (53%) on omega-3-acid ethyl esters [primary endpoint, HR 1.19; 95% CI: 0.93, 1.35]. In the persistent AF stratum, there were 19 (35%) events on placebo and 34 (52%) events on omega-3-acid ethyl esters [HR 1.63; 95% CI: 0.91, 2.18]. For both strata combined, the HR was 1.25; 95% CI: 1.00, 1.40. Although the clinical significance of these results is uncertain, there is a possible association between omega-3-acid ethyl esters and more frequent recurrences of symptomatic AF or flutter in patients with paroxysmal or persistent AF, particularly within the first 2 to 3 months of initiating therapy.

Omega-3-acid ethyl esters are not indicated for the treatment of AF or flutter.

6 ADVERSE REACTIONS

6.1 Clinical Trials Experience

Because clinical trials are conducted under widely varying conditions, adverse reaction rates observed in the clinical trials of a drug cannot be directly compared with rates in the clinical trials of another drug and may not reflect the rates observed in practice.

Adverse reactions reported in at least 3% of subjects treated with Omega-3-acid ethyl esters and at a greater rate than placebo based on pooled data across 23 clinical trials are listed in Table 1.

Table 1. Adverse Reactions Occurring at Incidence ≥3% and Greater than Placebo in Clinical Trials of Omega-3-Acid Ethyl Esters

Adverse Reaction* | Omega-3-Acid Ethyl Esters; (n = 655) |  | Placebo; (n = 370)
 | n | % | n | %
Eructation | 29 | 4 | 5 | 1
Dyspepsia | 22 | 3 | 6 | 2
Taste perversion | 27 | 4 | 1 | <1

*Trials included subjects with hypertriglyceridemia and severe hypertriglyceridemia.

Additional adverse reactions from clinical trials are listed below:

Digestive System

Constipation, gastrointestinal disorder and vomiting.

Metabolic and Nutritional Disorders

Increased ALT and increased AST.

Skin

Pruritus and rash.

6.2 Postmarketing Experience

In addition to adverse reactions reported from clinical trials, the events described below have been identified during post-approval use of omega-3-acid ethyl esters. Because these events are reported voluntarily from a population of unknown size, it is not possible to reliably estimate their frequency or to always establish a causal relationship to drug exposure.

The following events have been reported: anaphylactic reaction, hemorrhagic diathesis, urticaria.

7 DRUG INTERACTIONS

7.1 Anticoagulants or Other Drugs Affecting Coagulation

Some trials with omega-3-acids demonstrated prolongation of bleeding time. The prolongation of bleeding time reported in these trials has not exceeded normal limits and did not produce clinically significant bleeding episodes. Clinical trials have not been done to thoroughly examine the effect of omega-3-acid ethyl esters and concomitant anticoagulants. Patients receiving treatment with omega-3-acid ethyl esters and an anticoagulant or other drug affecting coagulation (e.g., anti-platelet agents) should be monitored periodically.

8 USE IN SPECIFIC POPULATIONS

8.1 Pregnancy

Risk Summary

The available data from published case reports and the pharmacovigilance database on the use of omega-3-acids ethyl esters in pregnant women are insufficient to identify a drug-associated risk for major birth defects, miscarriage, or adverse maternal or fetal outcomes. In animal studies, omega-3-acid ethyl esters given orally to female rats prior to mating through lactation did not have adverse effects on reproduction or development when given at doses 5 times the maximum recommended human dose (MRHD) of 4 grams/day, based on a body surface area comparison. Omega-3-acid ethyl esters given orally to rats and rabbits during organogenesis was not teratogenic at clinically relevant exposures, based on body surface area comparison (see Data).

The estimated background risk of major birth defects and miscarriage for the indicated population is unknown. In the U.S. general population, the estimated background risk of major birth defects and miscarriage in clinically recognized pregnancies is 2% to 4% and 15% to 20%, respectively.

Data

Animal Data: In female rats given oral doses of omega-3-acid ethyl esters (100, 600, or 2,000 mg/kg/day) beginning 2 weeks prior to mating through lactation, no adverse effects were observed at 2,000 mg/kg/day (5 times the MRHD based on body surface area [mg/m^2]). In a dose-ranging study, female rats given oral doses of omega-3-acid ethyl esters (1,000, 3,000, or 6,000 mg/kg/day) beginning 2 weeks prior to mating through Postpartum Day 7 had decreased live births (20% reduction) and pup survival to Postnatal Day 4 (40% reduction) at or greater than 3,000 mg/kg/day in the absence of maternal toxicity at 3,000 mg/kg/day (7 times the MRHD based on body surface area [mg/m^2]).

In pregnant rats given oral doses of omega-3-acid ethyl esters (1,000, 3,000, or 6,000 mg/kg/day) during organogenesis, no adverse effects were observed in fetuses at a maternally toxic dose (increased food consumption) of 6,000 mg/kg/day (14 times the MRHD based on body surface area [mg/m^2]). In pregnant rats given oral doses of omega-3-acid ethyl esters (100, 600, or 2,000 mg/kg/day) from Gestation Day 14 through Lactation Day 21, no adverse effects were observed at 2,000 mg/kg/day (5 times the MRHD based on body surface area [mg/m^2]).

In pregnant rabbits given oral doses of omega-3-acid ethyl esters (375, 750, or 1,500 mg/kg/day) during organogenesis, no adverse effects were observed in fetuses given 375 mg/kg/day (2 times the MRHD based on body surface area [mg/m^2]). However, at higher doses, increases in fetal skeletal variations and reduced fetal growth were evident at maternally toxic doses (reduced food consumption and body weight gain) greater than or equal to 750 mg/kg/day (4 times the MRHD), and embryolethality was evident at 1,500 mg/kg/day (7 times the MRHD).

8.2 Lactation

Risk Summary

Published studies have detected omega-3 fatty acids, including EPA and DHA, in human milk. Lactating women receiving oral omega-3 fatty acids for supplementation have resulted in higher levels of omega-3 fatty acids in human milk. There are no data available on the effects of omega-3 fatty acid ethyl esters on the breastfed infant or on milk production. The developmental and health benefits of breastfeeding should be considered along with the mother’s clinical need for omega-3-acids ethyl esters and any potential adverse effects on the breastfed child from omega-3-acids ethyl esters or from the underlying maternal condition.

8.4 Pediatric Use

Safety and effectiveness in pediatric patients have not been established.

8.5 Geriatric Use

A limited number of subjects older than 65 years were enrolled in the clinical trials of omega-3-acid ethyl esters. Safety and efficacy findings in subjects older than 60 years did not appear to differ from those of subjects younger than 60 years.

11 DESCRIPTION

Omega-3-acid ethyl esters, USP, a lipid-regulating agent, is supplied as a liquid-filled gel capsule for oral administration. Each 1-gram capsule of omega-3-acid ethyl esters contains at least 900 mg of the ethyl esters of omega-3 fatty acids sourced from fish oils. These are predominantly a combination of ethyl esters of eicosapentaenoic acid (EPA — approximately 465 mg) and docosahexaenoic acid (DHA — approximately 375 mg).

The empirical formula of EPA ethyl ester is C22H34O2, and the molecular weight of EPA ethyl ester is 330.51. The structural formula of EPA ethyl ester is:

The empirical formula of DHA ethyl ester is C24H36O2, and the molecular weight of DHA ethyl ester is 356.55. The structural formula of DHA ethyl ester is:

Omega-3-acid ethyl esters capsules USP also contain the following inactive ingredients: gelatin, glycerin and purified water. The imprinting ink contains the following: propylene glycol, shellac glaze and titanium dioxide.

12 CLINICAL PHARMACOLOGY

12.1 Mechanism of Action

The mechanism of action of omega-3-acid ethyl esters is not completely understood. Potential mechanisms of action include inhibition of acyl-CoA:1,2-diacylglycerol acyltransferase, increased mitochondrial and peroxisomal -oxidation in the liver, decreased lipogenesis in the liver, and increased plasma lipoprotein lipase activity. Omega-3-acid ethyl esters may reduce the synthesis of TG in the liver because EPA and DHA are poor substrates for the enzymes responsible for TG synthesis, and EPA and DHA inhibit esterification of other fatty acids.

12.3 Pharmacokinetics

Absorption

In healthy volunteers and in subjects with hypertriglyceridemia, EPA and DHA were absorbed when administered as ethyl esters orally. Omega-3-acids administered as ethyl esters induced significant, dose-dependent increases in serum phospholipid EPA content, though increases in DHA content were less marked and not dose-dependent when administered as ethyl esters.

Specific Populations

Age:Uptake of EPA and DHA into serum phospholipids in subjects treated with omega-3-acid ethyl esters was independent of age (younger than 49 years versus 49 years and older).

Male and Female Patients:Females tended to have more uptake of EPA into serum phospholipids than males. The clinical significance of this is unknown.

Pediatric Patients:Pharmacokinetics of omega-3-acid ethyl esters have not been studied.

Patients with Renal or Hepatic Impairment:omega-3-acid ethyl esters has not been studied in patients with renal or hepatic impairment.

Drug Interaction Studies

Simvastatin: In a 14-day trial of 24 healthy adult subjects, daily coadministration of simvastatin 80 mg with omega-3-acid ethyl esters 4 grams did not affect the extent (AUC) or rate (Cmax) of exposure to simvastatin or the major active metabolite, beta-hydroxy simvastatin at steady state.

Atorvastatin: In a 14-day trial of 50 healthy adult subjects, daily coadministration of atorvastatin 80 mg with omega-3-acid ethyl esters 4 grams did not affect AUC or Cmaxof exposure to atorvastatin, 2-hydroxyatorvastatin, or

4-hydroxyatorvastatin at steady state.

Rosuvastatin: In a 14-day trial of 48 healthy adult subjects, daily coadministration of rosuvastatin 40 mg with omega-3-acid ethyl esters 4 grams did not affect AUC or Cmaxof exposure to rosuvastatin at steady state.

In vitro studies using human liver microsomes indicated that clinically significant cytochrome P450-mediated inhibition by EPA/DHA combinations are not expected in humans.

13 NONCLINICAL TOXICOLOGY

13.1 Carcinogenesis, Mutagenesis, Impairment of Fertility

In a rat carcinogenicity study with oral gavage doses of 100, 600, and 2,000 mg/kg/day, males were treated with omega-3-acid ethyl esters for 101 weeks and females for 89 weeks without an increased incidence of tumors (up to 5 times human systemic exposures following an oral dose of 4 grams/day based on a body surface area comparison). Standard lifetime carcinogenicity bioassays were not conducted in mice.

Omega-3-acid ethyl esters were not mutagenic or clastogenic with or without metabolic activation in the bacterial mutagenesis (Ames) test with Salmonella typhimurium and Escherichia coli or in the chromosomal aberration assay in Chinese hamster V79 lung cells or human lymphocytes. Omega-3-acid ethyl esters were negative in the in vivo mouse micronucleus assay.

In a rat fertility study with oral doses of 100, 600, and 2,000 mg/kg/day, males were treated for 10 weeks prior to mating and females were treated for 2 weeks prior to mating and through lactation. No adverse effect on fertility was observed at 2,000 mg/kg/day (5 times the MRHD of 4 grams/day based on a body surface area [mg/m^2]).

14 CLINICAL STUDIES

14.1 Severe Hypertriglyceridemia

The effects of omega-3-acid ethyl esters 4 grams per day were assessed in 2 randomized, placebo-controlled, double-blind, parallel-group trials of 84 adult subjects (42 on omega-3-acid ethyl esters, 42 on placebo) with very high TG levels. Subjects whose baseline TG levels were between 500 and 2,000 mg/dL were enrolled in these 2 trials of 6 and 16 weeks’ duration. The median TG and LDL-C levels in these subjects were 792 mg/dL and 100 mg/dL, respectively. Median high-density lipoprotein cholesterol (HDL-C) level was 23.0 mg/dL.

The changes in the major lipoprotein lipid parameters for the groups receiving omega-3-acid ethyl esters or placebo are shown in Table 2.

1. Table 2. Median Baseline and Percent Change from Baseline in Lipid Parameters in Subjects with Severe Hypertriglyceridemia (≥500 mg/dL)

Parameter | Omega-3-Acid Ethyl Esters; n = 42 |  | Placebo; n = 42 |  | Difference
 | BL | % Change | BL | % Change
TG | 816 | -44.9 | 788 | +6.7 | -51.6
Non-HDL-C | 271 | -13.8 | 292 | -3.6 | -10.2
TC | 296 | -9.7 | 314 | -1.7 | -8/0
WLDL-C | 175 | -41.7 | 175 | -0.9 | -40.8
HDL-C | 22 | +9.1 | 24 | 0.0 | +9.1
LDL-C | 89 | +44.5 | 108 | -4.8 | +49.3

BL = Baseline (mg per dL); % Change = Median Percent Change from Baseline; Difference = Omega-3-acid ethyl esters Median % Change – Placebo Median % Change. TC = Total cholesterol.

VLDL-C = Very-low-density lipoprotein (VLDL) cholesterol.

Omega-3-acid ethyl esters 4 grams per day reduced median TG, VLDL-C, and non-HDL-C levels and increased median HDL-C from baseline relative to placebo. Treatment with omega-3-acid ethyl esters to reduce very high TG levels may result in elevations in LDL-C and non-HDL-C in some individuals. Patients should be monitored to ensure that the LDL-C level does not increase excessively.

The effect of omega-3-acid ethyl esters on the risk of pancreatitis has not been determined.

The effect of omega-3-acid ethyl esters on cardiovascular mortality and morbidity has not been determined.

16 HOW SUPPLIED/STORAGE AND HANDLING

Omega-3-acid ethyl esters capsules USP are supplied as 1 gram oblong, clear, soft gel capsules filled with slightly yellow to yellow liquid and imprinted with "PC25" in white ink. They are supplied in

NDC: 70518-3040-00

PACKAGING: 180 in 1 BOTTLE PLASTIC

Store at 20 °C to 25 °C (68 °to 77 °F) [See USP Controlled Room Temperature]. Do not freeze. Keep out of reach of children.

Protect from light.

Repackaged and Distributed By:

Remedy Repack, Inc.

625 Kolter Dr. Suite #4 Indiana, PA 1-724-465-8762

17 PATIENT COUNSELING INFORMATION

Advise the patient to read the FDA-approved patient labeling (Patient Information).

Information for Patients:

- Omega-3-acid ethyl esters capsules should be used with caution in patients with known sensitivity or allergy to fish and/or shellfish [see Warnings and Precautions (5.2)].
- Advise patients that use of lipid-regulating agents does not reduce the importance of adhering to diet [see Dosage and Administration (2)].
- Advise patients not to alter omega-3-acid ethyl esters capsules in any way and to ingest intact capsules only [see Dosage and Administration (2)].
- Instruct patients to take omega-3-acid ethyl esters capsules as prescribed. If a dose is missed, advise patients to take it as soon as they remember. However, if they miss one day of omega-3-acid ethyl esters capsules, they should not double the dose when they take it.

Repackaged By / Distributed By: RemedyRepack Inc.

625 Kolter Drive, Indiana, PA 15701

(724) 465-8762

Patient Information

OMEGA-3-ACID ETHYL ESTERS CAPSULES USP

Rx Only

What are omega-3-acid ethyl esters capsules?

Omega-3-acid ethyl esters capsules are a prescription medicine used along with a low fat and low cholesterol diet to lower very high triglyceride (fat) levels in adults.

It is not known if omega-3-acid ethyl esters capsules changes your risk of having inflammation of your pancreas (pancreatitis).

It is not known if omega-3-acid ethyl esters capsules prevents you from having a heart attack or stroke.

It is not known if omega-3-acid ethyl esters capsules is safe and effective in children.

Who should not take omega-3-acid ethyl esters capsules?

Do not take omega-3-acid ethyl esters capsulesif you are allergic to omega-3-acid ethyl esters or any of the ingredients in omega-3-acid ethyl esters capsules. See the end of this leaflet for a complete list of ingredients in omega-3-acid ethyl esters capsules.

Before taking omega-3-ethyl esters capsules, tell your healthcare provider about all your medical conditions, including if you:

- have diabetes.
- have a low thyroid problem (hypothyroidism).
- have a liver problem.
- have a pancreas problem.
- have a certain heart rhythm problem called atrial fibrillation or flutter.
- are allergic to fish or shellfish. It is not known if people who are allergic to fish or shellfish are also allergic to omega-3-acid ethyl esters capsules.
- are pregnant or plan to become pregnant. It is not known if omega-3-acid ethyl esters capsules will harm your unborn baby.
- are breastfeeding or plan to breastfeed. Omega-3-acid ethyl esters can pass into your breast milk. Talk to your healthcare provider about the best way to feed your baby if you take omega-3-acid ethyl esters capsules.

Tell your healthcare provider about all the medicines you take,including prescription and over-the-counter medicines, vitamins, and herbal supplements.

Omega-3-acid ethyl esters capsules can interact with certain other medicines that you are taking. Using omega-3-acid ethyl esters capsules with medicines that affect blood clotting (anticoagulants or blood thinners) may cause serious side effects.

How should I take omega-3-acid ethyl esters capsules?

- Take omega-3-acid ethyl esters capsules exactly as your healthcare provider tells you to take it.
- You should not take more than 4 capsules of omega-3-acid ethyl esters capsules each day. Either take all 4 capsules at one time, or 2 capsules two times a day.
- Do not change your dose or stop omega-3-acid ethyl esters capsules without talking to your healthcare provider.
- Take omega-3-acid ethyl esters capsules with food.
- Take omega-3-acid ethyl esters capsules whole. Do not break, crush, dissolve, or chew omega-3-acid ethyl esters capsules before swallowing. If you cannot swallow omega-3-acid ethyl esters capsules whole, tell your healthcare provider. You may need a different medicine.
- If you miss a dose of omega-3-acid ethyl esters capsules, take the missed dose as soon as you remember. If you miss one day of omega-3-acid ethyl esters capsules, do not double your dose the next time you take it.
- Your healthcare provider may start you on a cholesterol-lowing diet before giving you omega-3-acid ethyl esters capsules. Stay on this diet while taking omega-3-acid ethyl esters capsules.
- Your healthcare provider should do blood tests to check your triglyceride, bad cholesterol (LDL-C) and liver function (ALT and AST) levels while you take omega-3-acid ethyl esters capsules.

What are the possible side effects of omega-3-acid ethyl esters capsules?

Omega-3-acid ethyl esters capsules may cause serious side effects, including:

- changes in certain blood tests.Omega-3-acid ethyl esters capsules may cause an increase in the results of blood tests used to check your liver function and your bad cholesterol levels.
- increased risk of a heart rhythm problem in people who have a heart rhythm problem.Omega-3-acid ethyl esters capsules may cause an increase in the frequency of a heart rhythm problem (atrial fibrillation or flutter), especially in the first few months of taking omega-3-acid ethyl esters capsules, if you already have a heart rhythm problem.

The most common side effects of omega-3-acid ethyl esters capsules include:

- burping
- upset stomach
- a change in your sense of taste.

These are not all the possible side effects of omega-3-acid ethyl esters capsules. Call your doctor for medical advice about side effects. You may report side effects to FDA at 1-800-FDA-1088.

How should I store omega-3-acid ethyl esters capsules?

- Store omega-3-acid ethyl esters capsules at room temperature between 68°to 77°F (20°to 25°C).
- Do notfreeze omega-3-acid ethyl esters capsules.
- Safely throw away medicine that is out of date or no longer needed.

Keep omega-3-acid ethyl esters capsules and all medicines out of the reach of children.

General information about the safe and effective use of omega-3-acid ethyl esters capsules

Medicines are sometimes prescribed for purposes other than those listed in a Patient Information leaflet. Do not use omega-3-acid ethyl esters capsules for a condition for which it was not prescribed. Do not give omega-3-acid ethyl esters capsules to other people, even if they have the same symptoms you have. It may harm them. You can ask your healthcare provider or pharmacist for information about omega-3-acid ethyl esters capsules that is written for health professionals.

What are the ingredients in omega-3-acid ethyl esters capsules?

Active Ingredient: omega-3-acid ethyl esters, USP, mostly EPA and DHA

Inactive Ingredients: gelatin, glycerin and purified water. The imprinting ink contains the following: propylene glycol, shellac glaze and titanium dioxide.

This patient labeling has been approved by the U.S. Food and Drug Administration.

Repackaged and Distributed By:

Remedy Repack, Inc.

625 Kolter Dr. Suite #4 Indiana, PA 1-724-465-8762

PACKAGE LABEL

DRUG: OMEGA-3-ACID ETHYL ESTERS

GENERIC: OMEGA-3-ACID ETHYL ESTERS

DOSAGE: CAPSULE, LIQUID FILLED

ADMINSTRATION: ORAL

NDC: 70518-3040-0

COLOR: yellow

SHAPE: CAPSULE

SCORE: No score

SIZE: 25 mm

IMPRINT: PC25

PACKAGING: 180 in 1 BOTTLE, PLASTIC

ACTIVE INGREDIENT(S):

- OMEGA-3-ACID ETHYL ESTERS 1g in 1

INACTIVE INGREDIENT(S):

- GELATIN, UNSPECIFIED
- GLYCERIN
- WATER
- PROPYLENE GLYCOL
- SHELLAC
- TITANIUM DIOXIDE